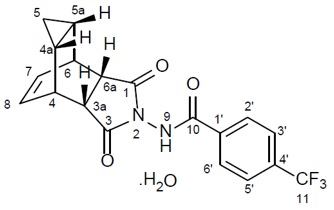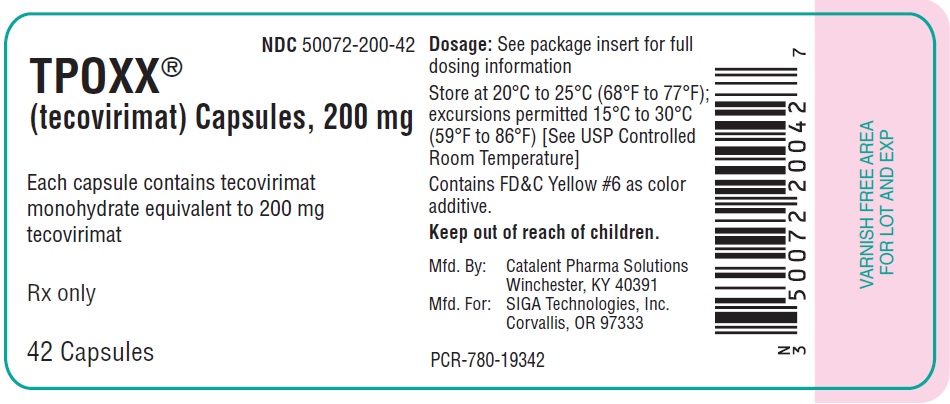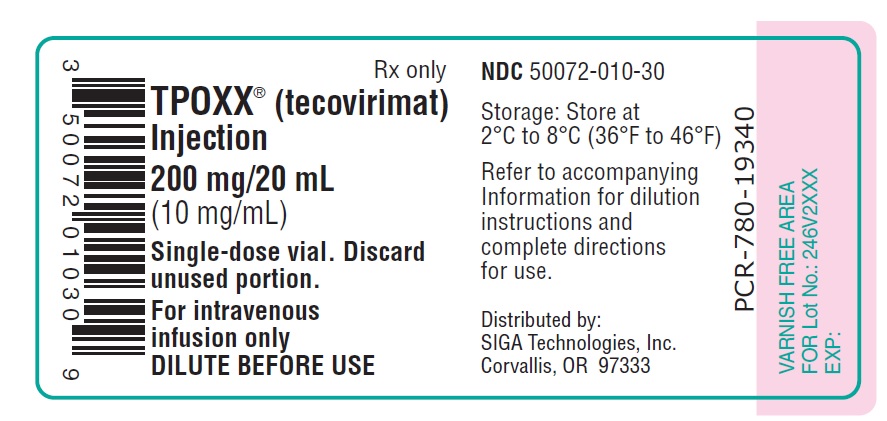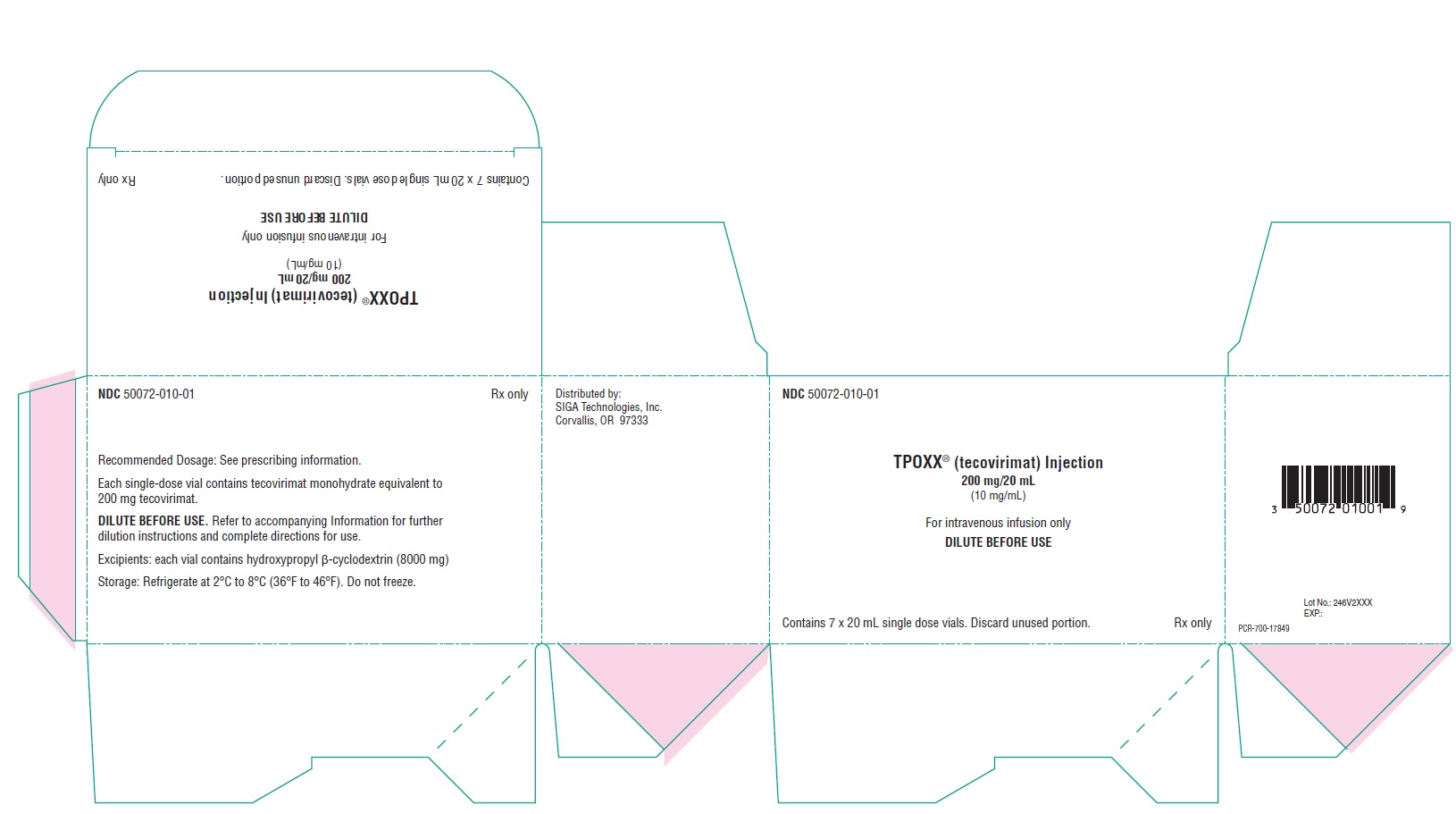 DRUG LABEL: TPOXX
NDC: 50072-010 | Form: INJECTION, SOLUTION, CONCENTRATE
Manufacturer: SIGA Technologies, Inc.
Category: prescription | Type: HUMAN PRESCRIPTION DRUG LABEL
Date: 20251231

ACTIVE INGREDIENTS: TECOVIRIMAT 10 mg/1 mL

HIGHLIGHTS OF PRESCRIBING INFORMATION

These highlights do not include all the information needed to use TPOXX®safely and effectively. See full prescribing information for TPOXX.
TPOXX (tecovirimat) capsules, for oral use
TPOXX (tecovirimat) injection for intravenous use
Initial U.S. Approval: 2018

1 INDICATIONS AND USAGE

TPOXX is an inhibitor of the orthopoxvirus VP37 envelope wrapping protein and is indicated for the treatment of human smallpox disease in adults and pediatric patients weighing at least 3 kg. (1.1)

Limitations of Use:

- The effectiveness of TPOXX for treatment of smallpox disease has not been determined in humans because adequate and well-controlled field trials have not been feasible, and inducing smallpox disease in humans to study the drug’s efficacy is not ethical. (1.2)
- TPOXX efficacy may be reduced in immunocompromised patients based on studies demonstrating reduced efficacy in immunocompromised animal models. (1.2)

2 DOSAGE AND ADMINISTRATION

- Pediatric and Adult Patientsweighing 40 kg or more (2.3) (Oral Dosing):
  - 40 kg to less than 120 kg: 600 mg of TPOXX every 12 hours for 14 days
  - 120 kg or more: 600 mg of TPOXX every 8 hours for 14 days
- Pediatrics and adult patients weighing 13 kg or more and those who cannot swallow capsules(2.3) (Oral Dosing):TPOXX Capsules can be administered by carefully opening the number of capsule noted below and mixing and administering the entire contents in 30 mL of liquid (e.g., milk, chocolate milk) or soft food (e.g., apple sauce, yogurt):
  - 13 kg to less than 25 kg: 200 mg (1 Capsule) of TPOXX every 12 hours for 14 days
  - 25 kg to less than 40 kg: 400 mg (2 Capsules) of TPOXX every 12 hours for 14 days
  - 40 kg to less than 120 kg: 600 mg (3 Capsules) of TPOXX every 12 hours for 14 days
  - 120 kg or more: 600 mg (3 capsules) every 8 hours for 14 days
- Patients weighing 3 kg and above(2.5) (Intravenous Dosing):
  - 3 kg to less than 35 kg: 6 mg/kg every 12 hours by intravenous infusion over 6 hours for up to 14 days
  - 35 kg to less than 120 kg: 200 mg every 12 hours by intravenous infusion over 6 hours for up to 14 days
  - 120 kg and above: 300 mg every 12 hours by intravenous infusion over 6 hours for up to 14 days
- Pediatric patients weighing 13 kg or more should be switched to TPOXX Capsules to complete the 14-day treatment course as soon as oral therapy can be tolerated.
- Administration Instruction for TPOXX Capsules:Take within 30 minutes after a full meal containing moderate or high fat. (2.1, 2.3)
- Administration Instructions for TPOXX Injection:Infuse over 6 hours via infusion pump. (2.5)
- See Full Prescribing Information for additional information on the administration and preparation of TPOXX Capsules and Injection. (2)

3 DOSAGE FORMS AND STRENGTHS

Capsules

- 200 mg of tecovirimat (2.4)

Injection

- A single-dose vial containing 200 mg of tecovirimat in 20 mL for further dilution prior to intravenous infusion. (3)

4 CONTRAINDICATIONS

- TPOXX capsules: None
- TPOXX injection: TPOXX Injection is contraindicated in patients with severe renal impairment (defined as creatinine clearance below 30 mL/min) (4, 5.2)

5 WARNINGS AND PRECAUTIONS

Hypoglycemia: Co-administration with repaglinide may cause hypoglycemia. Monitor blood glucose and monitor for hypoglycemic symptoms during co-administration. (5.1)

6 ADVERSE REACTIONS

The most common adverse reactions are:

- TPOXX Capsules (incidence ≥ 2%): headache, nausea, abdominal pain, and vomiting. (6.1)
- TPOXX Injection (incidence ≥ 4%): administration site reactions and headache. (6.1)

To report SUSPECTED ADVERSE REACTIONS, contact SIGA Technologies Inc. at 1-888-899-3472 or FDA at 1-800-FDA-1088 or www.fda.gov/medwatch.

7 DRUG INTERACTIONS

Consult the full prescribing information prior to and during treatment for potential drug interactions. (5.1, 7, 12.3)

8 USE IN SPECIFIC POPULATIONS

Lactation: Breastfeeding is not recommended in patients with smallpox. (8.2)

FULL PRESCRIBING INFORMATION

1 INDICATIONS AND USAGE

1.1 Treatment of Human Smallpox Disease

TPOXX®is indicated for the treatment of human smallpox disease caused by variola virus in adults and pediatric patients weighing at least 3 kg.

1.2 Limitations of Use

The effectiveness of TPOXX for treatment of smallpox disease has not been determined in humans because adequate and well-controlled field trials have not been feasible, and inducing smallpox disease in humans to study the drug’s efficacy is not ethical [see Clinical Studies (14)] .

TPOXX efficacy may be reduced in immunocompromised patients based on studies demonstrating reduced efficacy in immunocompromised animal models.

2 DOSAGE AND ADMINISTRATION

2.1 Important Dosing Instructions

It is recommended that patients 13 kg and above initiate oral treatment with TPOXX capsules if possible. If patients are unable to take oral TPOXX capsules or Drug-Food Preparation, treatment may be initiated with TPOXX injection as a 6 hour intravenous (IV) infusion. If IV treatment is necessary, conversion from IV to oral TPOXX is recommended as soon as oral treatment can be tolerated [see Dosage and Administration (2.3)] . In patients receiving an IV infusion, the first dose of oral treatment should be given at the time of and in place of the next scheduled IV dosing.

In patients receiving an oral treatment who subsequently require IV treatment, the first dose of IV infusion should be given at the time of and in place of the next scheduled oral dosing.

TPOXX capsules

Take TPOXX capsules within 30 minutes after a full meal containing moderate or high fat.

Missed Dose

If a dose of oral TPOXX is missed, the patient should take the dose as soon as possible and anytime up to 8 hours prior to the next scheduled dose. If less than 8 hours remain before the next scheduled dose, do not take the missed dose, and resume dosing at the next scheduled dose.

TPOXX injection

Administer TPOXX injection by IV infusion over 6 hours via an infusion pump. Must dilute TPOXX Injection prior to use [see Dosage and Administration (2.5)] .

2.2 Testing Before Initiating and During Treatment with TPOXX Injection

Determine creatinine clearance in all patients before starting TPOXX injection and monitor while receiving TPOXX injection as clinically appropriate [see Dosage and Administration (2.4), Contraindictions (4), Warnings and Precautions (5.2) and Use in Specific Populations (8.4, 8.6)] .

2.3 TPOXX Oral Dosage for Pediatric Patients Weighing at Least 13 kg and Adults

The recommended dosage of TPOXX capsules in pediatric patients weighing at least 13 kg and adults is displayed in Table 1 below.

Table 1: Recommended Dosage and Preparation Instructions for TPOXX Capsules in Pediatric Patients Weighing at Least 13 kg and Adults
Body Weight | Oral Dosage for 14 Daysa
Body Weight | Dosage (Number of Capsules) | Drug Food Preparation for Patients Who Cannot Swallow Capsules
13 kg to less than 25 kg | 200 mg (1 capsule) every 12 hours | Carefully open the required number of capsules and mix contents of capsule(s) of TPOXX with 30 mL of liquid (e.g., milk, chocolate milk) or soft food (e.g., apple sauce, yogurt). The entire mixture should be administered within 30 minutes of its preparation.
25 kg to less than 40 kg | 400 mg (2 capsules) every 12 hours | Carefully open the required number of capsules and mix contents of capsule(s) of TPOXX with 30 mL of liquid (e.g., milk, chocolate milk) or soft food (e.g., apple sauce, yogurt). The entire mixture should be administered within 30 minutes of its preparation.
40 kg to less than 120 kg | 600 mg (3 capsules) every 12 hours | Carefully open the required number of capsules and mix contents of capsule(s) of TPOXX with 30 mL of liquid (e.g., milk, chocolate milk) or soft food (e.g., apple sauce, yogurt). The entire mixture should be administered within 30 minutes of its preparation.
120 kg and above | 600 mg (3 capsules) every 8 hours | Carefully open the required number of capsules and mix contents of capsule(s) of TPOXX with 30 mL of liquid (e.g., milk, chocolate milk) or soft food (e.g., apple sauce, yogurt). The entire mixture should be administered within 30 minutes of its preparation.
aTPOXX capsules should be taken within 30 minutes after a full meal containing moderate or high fat [see Clinical Pharmacology (12.3)]

2.4 Renal Impairment

TPOXX injection is contraindicated in patients with creatinine clearance below 30 mL per minute [see Contraindictions (4)] .

2.5 Dosage and Administration of TPOXX Injection for Intravenous Infusion

The recommended dosage of TPOXX injection in pediatric patients weighing at least 3 kg and adults is displayed in Table 2below.

TPOXX injection is supplied in a single-dose clear glass vial containing 200 mg/20 mL (10 mg/mL). Parenteral drug products must be inspected visually for particulate matter and discoloration prior to administration, whenever solution and container permit. To administer:

- Use aseptic technique when preparing TPOXX injection.
- Withdraw the quantity of TPOXX injection (Table 2), add this volume to the syringe then dilute with two equal parts of either 0.9% (w/v) sodium chloride injection (normal saline) or 5% (w/v) dextrose injection in a syringe of suitable size. Injection with diluents other than 0.9% sodium chloride or 5% dextrose solution has not been studied. NOT FOR IV BOLUS INJECTION. Do not use prefilled infusion bags for product preparation and administration.
- The diluted TPOXX injection may be stored refrigerated (2°C - 8°C) for up to 24 hours or at room temperature (15°C - 25°C) for up to 4 hours.
- Gently swirl the syringe of in-use solution prior to inserting into the syringe pump and infuse over 6 hours every 12 hours for 14 days.
- Do not re-use the single-dose vial once it has been punctured.

Table 2: Recommended Pediatric and Adult Dosage and Preparation Instructions TPOXX Injection for IV Infusiona
Body Weight | Dosage for up to 14 days | Volume of TPOXX Injectionb | Volume of Diluentc
3 kg to less than 35 kg | 6 mg/kg every 12 hours by intravenous infusion over 6 hoursa | 0.6 mL/kg | 1.2 mL/kg
35 kg to less than 120 kg | 200 mg every 12 hours by intravenous infusion over 6 hours | 20 mL | 40 mL
120 kg and aboved | 300 mg every 12 hours by intravenous infusion over 6 hours | 30 mL | 60 mL
aPatients weighing at least 13 kg should be switched to TPOXX Capsules to complete the 14 day treatment course as soon as oral therapy can be tolerated.
b10 mg/mL TPOXX solution containing 40% hydroxypropyl betadex (8 g per vial) with water for injection [see Dosage Forms and Strengths (3)]
cDiluent is either 0.9% (w/v) sodium chloride injection or 5% (w/v) dextrose injection solution.
dDepending on size of syringe available with syringe pump system, two separate syringes may be needed for each 6 hour administration.

3 DOSAGE FORMS AND STRENGTHS

TPOXX Capsules

TPOXX capsules are hard gelatin with an opaque orange body imprinted in white ink with “SIGA” followed by the SIGA logo followed by “®”, and an opaque black cap imprinted in white ink with “ST-246®”, containing white to off-white powder. Each capsule contains 200 mg of tecovirimat.

TPOXX Injection

TPOXX injection: 200 mg/20 mL (10 mg/mL) of tecovirimat as a clear, colorless to pale yellow solution in a single-dose vial for further dilution.

4 CONTRAINDICATIONS

TPOXX Capsules:

None.

TPOXX Injection:

The excipient hydroxypropyl-β-cyclodextrin is eliminated through glomerular filtration. Therefore, TPOXX Injection is contraindicated in patients with severe renal impairment (defined as creatinine clearance below 30 mL/min) [see Warnings and Precautions (5.2) and Use in Specific Populations (8.6)] .

5 WARNINGS AND PRECAUTIONS

5.1 Hypoglycemia When Co-Administered with Repaglinide

Co-administration of repaglinide and tecovirimat may cause mild to moderate hypoglycemia. Monitor blood glucose and monitor for hypoglycemic symptoms when administering TPOXX with repaglinide [see Drug Interactions (7.1) and Clinical Pharmacology (12.3)] .

In a drug interaction study, 10 of 30 healthy subjects experienced mild (6 subjects) or moderate (4 subjects) hypoglycemia following co-administration of repaglinide (2 mg) and TPOXX. Symptoms resolved in all subjects after intake of food and/or oral glucose.

5.2 Risks of Hydroxypropyl-β-Cyclodextrin Excipient for Patients with Renal Insufficiency and Pediatric Patients < 2 Years of Age

Patients with renal insufficiency

TPOXX Injection: In healthy patients and in patients with mild to severe renal insufficiency, the majority of an 8 g dose of hydroxypropyl-β-cyclodextrin (per 200 mg tecovirimat/20 mL solution) is eliminated in the urine. It is known that clearance of hydroxypropyl-β-cyclodextrin is reduced in patients with mild, moderate, and severe renal impairment, resulting in higher exposure to hydroxypropyl-β-cyclodextrin; in these patients, half-life values are increased over normal values by approximately two-, four-, and six-fold, respectively. In these patients, successive infusions may result in accumulation of hydroxypropyl-β-cyclodextrin until steady state is reached.

In patients with mild (defined as creatinine clearance 60-89 mL/min) and moderate (defined as creatinine clearance 30-59 mL/min) renal impairment, TPOXX Injection should be used with caution. Creatinine clearance should be closely monitored and, if renal toxicity is suspected, consideration should be given to administering TPOXX orally if possible or to using an alternative medication. TPOXX Injection is contraindicated in patients with severe renal impairment (creatinine clearance 30 mL/min) [see Contraindictions (4) and Clinical Pharmacology (12.3)] .

Pediatric patients

TPOXX Injection: In pediatric patients less than 2 years of age, there are limited data regarding the use of hydroxypropyl-β-cyclodextrin. Given that renal tubular function rapidly matures over the first few years of life, clearance of hydroxypropyl-β-cyclodextrin may be reduced in young pediatric patients, resulting in higher exposure to hydroxypropyl-β-cyclodextrin. TPOXX Injection should be used with caution in this population given that animal studies have shown potential for nephrotoxicity at very high exposure levels of hydroxypropyl-β-cyclodextrin. Given the potential for drug accumulation due to renal immaturity in pediatric patients less than 2 years, monitoring of renal function after treatment is recommended [see Use in Specific Populations (8.4) and Clinical Pharmacology (12.3)] .

6 ADVERSE REACTIONS

6.1 Clinical Trials Experience

Because clinical trials are conducted under widely varying conditions, adverse reaction rates observed in the clinical trials of a drug cannot be directly compared to rates in the clinical trials of another drug and may not reflect the rates observed in practice.

The safety of TPOXX has not been studied in patients with smallpox disease.

TPOXX Clinical Trial (Oral Administration)

The safety of TPOXX was evaluated in 359 healthy adult subjects ages 18-79 years in a Phase 3 clinical trial. Of the subjects who received at least one 600 mg dose of TPOXX, 59% were female, 69% were White, 28% were Black/African American, 1% were Asian, and 12% were Hispanic or Latino. Ten percent of the subjects who participated in the study were age 65 or older. Of these 359 subjects, 336 subjects received at least 23 of 28 doses of 600 mg TPOXX in a twice daily (every 12 hours) regimen for 14 days.

Most Frequently Reported Adverse Reactions

The most frequently reported adverse reactions were headache and nausea. Adverse reactions that occurred in at least 2% of subjects in the TPOXX treatment group are shown in Table 3.

Table 3: Treatment-Related Adverse Reactions Reported in ≥ 2% of Healthy Adult Subjects Receiving at Least One Dose of TPOXX Capsules 600 mg
Adverse Reaction | TPOXX 600 mg N = 359 (%) | Placebo N = 90 (%)
Headache | 12 | 8
Nausea | 5 | 4
Abdominal paina | 2 | 1
Vomiting | 2 | 0
aIncludes abdominal pain, abdominal pain upper, abdominal distension, abdominal discomfort, abdominal pain
lower, epigastric pain

Adverse Reactions Leading to Discontinuation of TPOXX

Six subjects (2%) had their treatment with TPOXX discontinued due to adverse reactions. Each of these subject’s adverse reactions (with severity) is listed below:

- EEG change, abnormal
- Mild upset stomach, dry mouth, decreased concentration and dysphoria
- Mild nausea and fever, moderate diarrhea, severe headache
- Mild palpable purpura
- Mild nausea, fever and chills
- Mild facial redness, facial swelling and pruritus

Less Common Adverse Reactions

Clinically significant adverse reactions that were reported in <2% of subjects exposed to TPOXX and at rates higher than subjects who received placebo are listed below:

- Gastrointestinal: dry mouth, chapped lips, dyspepsia, eructation, oral paresthesia
- General and administration site: pyrexia, pain, chills, malaise, thirst
- Investigations: abnormal electroencephalogram, hematocrit decreased, hemoglobin decreased, heart rate increased
- Musculoskeletal and connective tissue: arthralgia, osteoarthritis
- Nervous system: migraine, disturbance in attention, dysgeusia, paresthesia
- Psychiatric: depression, dysphoria, irritability, panic attack
- Respiratory, Thoracic and Mediastinal Disorders: oropharyngeal pain
- Skin and subcutaneous tissue: palpable purpura, rash, pruritic rash, facial redness, facial swelling, pruritus

TPOXX Clinical Trial (Intravenous Administration)

The safety of multiple doses of 240 mg of TPOXX injection for IV infusion was evaluated in 26 healthy adult subjects ages 23-62 years, inclusive. An additional 6 subjects received placebo. TPOXX injection was administered over a 6 hour period via infusion pump twice daily (every 12 hours) for 7 days. Of the 26 subjects administered TPOXX, 42% were female, 69% were White, 23% were Black/African American, and 42% were Hispanic or Latino.

Most Frequently Reported Adverse Reactions

The most frequently reported adverse reactions included infusion site pain, infusion site swelling, infusion site erythema, infusion site extravasation, and headache. Adverse reactions that occurred in at least 4% of subjects in the TPOXX treatment group are shown in Table 4.

Table 4: Treatment-Related Adverse Reactions Reported in ≥ 4% of Healthy Adult Subjects Receiving at Least One Dose of TPOXX Injection 240 mg
 | TPOXX 240 mg N = 26 (%) | Placebo N = 6 (%)
Infusion Site Pain | 73 | 67
Infusion Site Swelling | 39 | 67
Infusion Site Erythema | 23 | 67
Infusion Site Extravasation | 19 | 50
Headache | 15 | 0

Adverse Reactions Leading to Discontinuation of TPOXX Injection

Three subjects (12%) had their treatment with TPOXX injection discontinued due to adverse reactions. One subject had two adverse reactions. Each of these subject’s adverse reactions (with severity) are listed below:

- Moderate Infusion site extravasation
- Mild Infusion site extravasation
- Mild Infusion site swelling and mild infusion site pain

Less Common Adverse Reactions

Clinically significant adverse reactions that were reported in <4% of subjects exposed to TPOXX injection and at rates higher than subjects who received placebo are listed below:

- General and administration site: infusion site discomfort, infusion site edema
- Musculoskeletal and connective tissue: myalgia, arthritis, back pain, muscle tightness
- Gastrointestinal: diarrhea
- Eye: photophobia
- Skin and Subcutaneous Tissue: pruritus generalized

7 DRUG INTERACTIONS

7.1 Effect of TPOXX on Other Drugs

Tecovirimat is a weak inducer of cytochrome P450 (CYP)3A and a weak inhibitor of CYP2C8 and CYP2C19. However, the effects are not expected to be clinically relevant for most substrates of those enzymes based on the magnitude of interactions and the duration of treatment of TPOXX.

Table 5provides a listing of established or significant drug interactions and clinical recommendations for select sensitive substrates [see Warnings and Precautions (5.1) and Clinical Pharmacology (12.3)] .

Table 5: Significant Drug Interactions with Effect of TPOXX on Other Drugs
Concomitant Drug Class: Drug Name | Effect on Concentrationa | Clinical Effect/Recommendation
Blood Glucose-Lowering Agent:
Repaglinideb | ↑ repaglinide | Monitor blood glucose and monitor for hypoglycemic symptoms in patients when TPOXX is co-administered with repaglinide [see Warnings and Precautions (5.1)] .
CNS Depressant:
Midazolamb | ↓ midazolam | Monitor for effectiveness of midazolam.
a↓ = decrease, ↑ = increase
bThese interactions have been studied in healthy adults.

7.2 Effect of Other drugs on TPOXX

Co-administration of phosphate binders with tecovirimat increases tecovirimat bioavailability. Table 6provides a listing of established drug interactions and clinical recommendations for select phosphate binders [see Clinical Pharmacology (12.3)] .

Table 6: Significant Drug Interactions with Effect of Other Drugs on TPOXX
Concomitant Drug Class: Drug Name | Effect on Concentrationa | Clinical Effect/Recommendation
Phosphate Bindersb:
Calcium acetate Lanthanum carbonate Sevelamer carbonate Sucroferric oxyhydroxide | ↑ tecovirimat | Monitor for signs or symptoms of adverse effects when TPOXX is co-administered with phosphate binders [see Overdose (10)] .
a↑ = increase
bThese interactions have been studied in healthy adults.

7.3 Drugs Without Clinically Significant Interactions With TPOXX

Based on a drug interaction study, no clinically significant drug interactions have been observed when TPOXX is co-administered with bupropion, flurbiprofen, or omeprazole [see Clinical Pharmacology (12.3)] .

7.4 Vaccine Interactions

No vaccine-drug interaction studies have been performed in human subjects. Some animal studies have indicated that co-administration of TPOXX at the same time as live smallpox vaccine (vaccinia virus) may reduce the immune response to the vaccine. The clinical impact of this interaction on vaccine efficacy is unknown.

8 USE IN SPECIFIC POPULATIONS

8.1 Pregnancy

Risk Summary

There are no available data on the use of tecovirimat in pregnant individuals to evaluate for a drug-associated risk of major birth defects, miscarriage, and other adverse maternal and fetal outcomes.

In animal reproduction studies, no embryofetal developmental toxicity was observed in mice during the period of organogenesis at tecovirimat exposures (area under the curve [AUC]) up to 23 times higher than human exposure at the recommended human dose (RHD). In rabbits, no embryofetal developmental toxicity was observed during organogenesis at tecovirimat exposures (AUC) less than human exposures at the RHD. In a mouse pre-/post-natal development study, no toxicities were observed at maternal tecovirimat exposures up to 24 times higher than human exposure at the RHD (see Data).

The background risk of major birth defects and miscarriage for the indicated population is unknown, and the estimated background risk of miscarriage for the indicated population is higher than the general population. All pregnancies have a background risk of birth defect, loss or other adverse outcomes. In the U.S. general population, the estimated background risk of major birth defects and miscarriage in clinically recognized pregnancies is 2-4% and 15-20%, respectively.

Data

Animal Data

Tecovirimat was administered orally to pregnant mice at doses up to 1,000 mg/kg/day from gestation Days 6-15. No embryofetal toxicities were observed at doses up to 1,000 mg/kg/day (approximately 23 times higher than human exposure at the RHD).

Tecovirimat was administered orally to pregnant rabbits at doses up to 100 mg/kg/day from gestation Days 6-19. No embryofetal toxicities were observed at doses up to 100 mg/kg/day (0.4 times the human exposure at the RHD).

In the pre-/post-natal development study, tecovirimat was administered orally to pregnant mice at doses up to 1,000 mg/kg/day from gestation Day 6 to post-natal Day 20. No toxicities were observed at doses up to 1,000 mg/kg/day (approximately 24 times higher than human exposure at the RHD).

8.2 Lactation

Risk Summary

Because of the potential for variola virus transmission through direct contact with the breastfed infant, breastfeeding is not recommended in patients with smallpox. There are no data on the presence of tecovirimat in human milk, the effects of the drug on the breastfed infant, or on milk production. Tecovirimat was present in animal milk (see Data). When a drug is present in animal milk, it is likely to be present in human milk.

Data

In a lactation study at doses up to 1,000 mg/kg/day, mean tecovirimat milk to plasma ratios up to approximately 0.8 were observed at 6 and 24 hours post-dose when administered orally to mice on lactation Day 10 or 11.

8.3 Females and Males of Reproductive Potential

Infertility

There are no data on the effect of tecovirimat on human fertility. Decreased fertility due to testicular toxicity was observed in male mice [see Nonclinical Toxicology (13.1)] .

8.4 Pediatric Use

As in adults, the effectiveness of TPOXX in pediatric patients is based solely on efficacy studies in animal models of orthopoxvirus disease. As exposure of healthy pediatric subjects to TPOXX with no potential for direct clinical benefit is not ethical, pharmacokinetic simulation was used to derive dosing regimens that are predicted to provide pediatric patients with exposures comparable to the observed exposure in adults receiving 600 mg orally twice daily (every 12 hours) or 200 mg intravenously twice daily (every 12 hours). The dosage for pediatric patients is based on weight [see Dosage and Administration (2.2) and Clinical Pharmacology (12.3)] .

TPOXX Injection:

There are limited data regarding the use of hydroxypropyl-β-cyclodextrin, an ingredient in TPOXX injection, in pediatric patients less than 2 years of age. Given the potential for drug accumulation due to renal immaturity in pediatric patients less than 2 years, monitoring of renal function after treatment is recommended [see Warnings and Precautions (5.2) and Clinical Pharmacology (12.3)] .

8.5 Geriatric Use

Clinical studies of TPOXX did not include sufficient numbers of subjects aged 65 and over to determine whether the safety profile of TPOXX is different in this population compared to younger subjects. Of the 359 subjects in the clinical study of TPOXX, 10% (36/359) were ≥ 65 years of age, and 1% (4/359) were ≥ 75 years of age. No alteration of dosing is needed for patients ≥ 65 years of age [see Clinical Pharmacology (12.3)] .

8.6 Renal Impairment

TPOXX Capsules:

No dosage adjustment is required for patients with mild, moderate or severe renal impairment or patients with end stage renal disease (ESRD) requiring hemodialysis [see Clinical Pharmacology (12.3)] .

TPOXX Injection:

Hydroxypropyl-β-cyclodextrin, an ingredient in TPOXX injection, when administered intravenously, is eliminated through glomerular filtration. No dosage adjustment is required for patients with mild (creatinine clearance 60-89 mL/min) or moderate (creatinine clearance 30-59 mL/min) renal impairment. TPOXX Injection is contraindicated in patients with severe renal impairment (creatinine clearance below 30 mL/min) [see Contraindictions (4)] .

8.7 Hepatic Impairment

No dosage adjustment is required for patients with mild, moderate or severe hepatic impairment (Child Pugh Class A, B, or C) [see Clinical Pharmacology (12.3)] .

10 OVERDOSAGE

There is no clinical experience with overdosage of TPOXX. In case of overdosage, monitor patients for any signs or symptoms of adverse effects. Hemodialysis will not significantly remove TPOXX in overdosed patients.

11 DESCRIPTION

TPOXX capsules and TPOXX injection contains tecovirimat, an inhibitor of the orthopoxvirus VP37 envelope wrapping protein.

TPOXX (tecovirimat) capsules, for oral use are immediate release capsules containing tecovirimat monohydrate equivalent to 200 mg of tecovirimat for oral administration. The capsules include the following inactive ingredients: colloidal silicon dioxide, croscarmellose sodium, hydroxypropyl methyl cellulose, lactose monohydrate, magnesium stearate, microcrystalline cellulose, and sodium lauryl sulfate. The capsule shell is composed of gelatin, FD&C blue #1, FD&C red #3, FD&C yellow #6, and titanium dioxide.

TPOXX (tecovirimat) injection, for intravenous use is a sterile, colorless to pale yellow solution free of visible particles that is intended for intravenous use following dilution. Tecovirimat injection is available in a single-dose vial containing 200 mg/20 mL (10 mg/mL) of tecovirimat and 8,000 mg (400 mg/mL) of Hydroxypropyl Betadex, NF (hydroxypropyl β-cyclodextrin) and Water for Injection, USP/NF.

Tecovirimat monohydrate is a white to off-white crystalline solid with the chemical name Benzamide, N-[(3a R,4 R,4a R,5a S,6 S,6a S)-3,3a,4,4a,5,5a,6,6a-octahydro-1,3-dioxo-4,6 ethenocycloprop[f]isoindol-2(1H)-yl]-4-(trifluoromethyl), rel-(monohydrate). The chemical formula is C19H15F3N2O3·H2O representing a molecular weight of 394.35 g/moL. The molecular structure is as follows:

Tecovirimat monohydrate is practically insoluble in water and across the pH range of 2.0-6.5 (< 0.1 mg/mL).

12 CLINICAL PHARMACOLOGY

12.1 Mechanism of Action

Tecovirimat is an antiviral drug against variola (smallpox) virus [see Microbiology (12.4)] .

12.2 Pharmacodynamics

Cardiac Electrophysiology

TPOXX does not prolong the QT interval to any clinically relevant extent at the anticipated therapeutic exposure.

12.3 Pharmacokinetics

At the recommended oral dosage of 600 mg every 12 hours administered in healthy adults weighing less than 120 kg, the mean steady-state values of tecovirimat AUC0-24hr, Cmax, and Ctau/troughare 29816 hr•ng/mL (n, CV: 43, 34%), 2159 ng/mL (n, CV: 46, 32%), and 845 ng/mL (n, CV: 45, 47%), respectively. At the recommended intravenous dosage of 200 mg every 12 hours administered by IV infusion over 6 hours in healthy adults, the mean steady-state values of tecovirimat AUC0-24hr, Cmax, and Cminare 39405 hr•ng/mL (n, CV: 22, 23%), 2630 ng/mL (n, CV: 22, 22%), and 747 ng/mL (n, CV: 22, 29%). Refer to Table 7for pharmacokinetic parameters of tecovirimat. Tecovirimat steady-state is achieved by Day 4-6.

Table 7: Pharmacokinetic Properties of Tecovirimat
Absorption | 200 mg intravenous | 600 mg oral
Median Tmax(h) (Range) | 6 (6-6.5) | 6 (2-24)a
Effect of food (relative to fasting) | NA | ↑39%b
Distribution
% Bound to human plasma proteins | 77-82
Blood-to-plasma ratio (drug or drug-related materials) | 0.62-0.90
Volume of distribution (Vz or Vz/F, L) (CV%) | 383 (46%) | 1030
Metabolism
Metabolic pathwaysc | Hydrolysis, UGT1A1d, UGT1A4
Elimination
Major route of elimination | Metabolism
Clearance (CL or CL/F, L/hr) (CV%) | 13 (23%) | 31
t1/2(h)e(CV%) | 21 (45%) | 19 (29%)
% of dose excreted in urinef | NA | 73, predominantly as metabolites
% of dose excreted in fecesf | NA | 23, predominantly as tecovirimat
aValue reflects administration of drug with food.
bValue refers to mean systemic exposure (AUC24hr). Meal: ~ 600 kcal, ~ 25 g fat.
cTecovirimat is metabolized by hydrolysis of the amide bond and glucuronidation. The following inactive
metabolites were detected in plasma: M4 (N-{3,5-dioxo-4-azatetracyclo[5.3.2.0{2,6}.0{8,10}]dodec-11-en-4-
yl}amine), M5 (3,5 dioxo-4-aminotetracyclo[5.3.2.0{2,6}.0{8,10}]dodec-11-ene), and TFMBA
(4 (trifluoromethyl) benzoic acid)
dUridine diphosphate (UDP)-glucuronosyl transferase (UGT) enzymes
et1/2value refers to mean terminal plasma half-life.
fSingle dose administration of [^14C]-tecovirimat in mass balance study.
KEY: NA = Not Applicable or Not Available

Comparison of Animal and Human PK Data to Support Effective Human Dose Selection

Because the effectiveness of TPOXX cannot be tested in humans, a comparison of tecovirimat exposures achieved in healthy human subjects to those observed in animal models of orthopoxvirus infection (nonhuman primates and rabbits infected with monkeypox virus and rabbitpox virus, respectively) in therapeutic efficacy studies was necessary to support the dosage regimen of 600 mg every 12 hours for treatment of smallpox disease in humans. Humans achieve greater systemic exposure (AUC, Cmax, and Cmin) of tecovirimat following a dose of 600 mg every 12 hours when compared to the therapeutic exposures in these animal models.

Specific Populations

No clinically significant differences in the pharmacokinetics of tecovirimat were observed based on age, sex, ethnicity, renal impairment (based on estimated GFR), or hepatic impairment (Child Pugh Scores A, B or C). At the 600 mg twice-daily dosage, tecovirimat exposure was reduced in adult subjects weighing more than 120 kg compared to the exposures in adult subjects weighing less than 120 kg. Specifically, in 34 adult subjects weighing more than 120 kg who received 600 mg TPOXX orally every 12 hours, the observed mean steady state values of AUC0-24hr, Cmax, and Ctroughwere 19500 hr•ng/mL (CV: 23%), 1300 ng/mL (CV: 29%), and 585 ng/mL (CV: 31%), respectively.

Pediatric Patients

TPOXX pharmacokinetics has not been evaluated in pediatric patients. The recommended pediatric dosing regimen is expected to produce tecovirimat exposures that are comparable to those in adult subjects based on a population pharmacokinetic modeling and simulation approach [see Dosage and Administration (2.2) and Use in Specific Populations (8.4)] .

Hydroxypropyl-β-cyclodextrin, when administered intravenously, is eliminated through glomerular filtration which may be reduced in pediatric patients with renal immaturity [see Warnings and Precautions (5.2) and Use in Specific Populations (8.4)] .

Drug Interaction Studies

The effect of tecovirimat on the exposure of co-administered drugs are shown in Table 8. The effect of co-administered drugs on the exposure of tecovirimat are shown in Table 9.

Table 8: Drug Interactions – Changes in Pharmacokinetic Parameters for Co-Administered Drug in the Presence of TPOXXa
Co-Administered Drug | Dose of Co-Administered Drug (mg) | N | Mean Ratio (90% CI) of Co-Administered Drug PK With/Without TPOXX No Effect = 1.00
Co-Administered Drug | Dose of Co-Administered Drug (mg) | N | Cmax | AUCinf
Flurbiprofen + omeprazole + midazolamb | omeprazole 20, single dose | 24 | 1.87 (1.51, 2.31) | 1.73 (1.36, 2.19)
Flurbiprofen + omeprazole + midazolamb | midazolam 2, single dose | 24 | 0.61 (0.54, 0.68) | 0.68 (0.63, 0.73)
Repaglinide | 2, single dose | 30 | 1.27 (1.12, 1.44) | 1.29 (1.19, 1.40)
Bupropion | 150, single dose | 24 | 0.86 (0.79, 0.93) | 0.84 (0.78, 0.89)
aAll interaction studies conducted in healthy volunteers with tecovirimat 600 mg twice daily (every 12 hours).
bComparison based on exposures when administered as flurbiprofen + omeprazole + midazolam.

No pharmacokinetic changes were observed for the following drug when co-administered with tecovirimat: flurbiprofen.

Cytochrome P450 (CYP) Enzymes: Tecovirimat is a weak inhibitor of CYP2C8 and CYP2C19, and a weak inducer of CYP3A4. Tecovirimat is not an inhibitor or an inducer of CYP2B6 or CYP2C9.

Table 9: Drug Interactions – Changes in TPOXX Pharmacokinetic Parameters in the Presence of Co-Administered Druga
Co-Administered Drug | Dose of Co-Administered Drug (mg) | Nb | Mean Ratio (90% CI) of TPOXX PK With/Without Co-Administered Drug No Effect = 1.00
Co-Administered Drug | Dose of Co-Administered Drug (mg) | Nb | Cmax | AUC0-24 hour
Phosphate binders | Sevelamer carbonate (1600 mg, single dose) | 39 | 1.16 (1.08, 1.26) | 1.26 (1.17, 1.36)
Phosphate binders | Sucroferric oxyhydroxide (500 mg, single dose) | 37 | 1.15 (1.06, 1.24) | 1.20 (1.11, 1.29)
Phosphate binders | Calcium acetate (1334 mg, single dose) | 37 | 1.09 (1.01, 1.18) | 1.16 (1.07, 1.25)
Phosphate binders | Lanthanum carbonate (500 mg, single dose) | 38 | 1.21 (1.12, 1.30) | 1.22 (1.13, 1.32)
aAll interaction studies conducted in healthy volunteers with tecovirimat 600 mg twice daily (every 12 hours) taken with a meal (consisting of approximately 600 calories and 25 g fat).
bNumber of subjects with reportable PK values when TPOXX was co-administered with phosphate binder.

The relative bioavailability indicated an increase in peak and total systemic exposure (Cmax and AUCs) when 600 mg TPOXX was orally administered with 4 different phosphate binders (1600 mg sevelamer carbonate, 500 mg sucroferric oxyhydroxide, 1334 mg calcium acetate, 500 mg lanthanum carbonate) compared to TPOXX administered alone.

In Vitro Studies Where Drug Interaction Potential Was Not Further Evaluated Clinically

CYP Enzymes:Tecovirimat is not an inhibitor of CYP1A2, CYP2D6, CYP2E1 or CYP3A4, and is not an inducer of CYP1A2. Tecovirimat is not a substrate for CYP1A2, CYP2B6, CYP2C8, CYP2C9, CYP2C19, CYP2D6 or CYP3A4.

UGT Enzymes:Tecovirimat is a substrate of UGT1A1 and UGT1A4.

Transporter Systems:Tecovirimat inhibited Breast Cancer Resistance Protein (BCRP) in vitro.

Tecovirimat is not an inhibitor of P-glycoprotein (P-gp), organic anion transporting polypeptides 1B1 and 1B3 (OATP1B1 and OATP1B3), organic anion transporter 1 (OAT1), OAT3, and organic cation transporter 2 (OCT2). Tecovirimat is not a substrate for P-gp, BCRP, OATP1B1, and OATP1B3.

12.4 Microbiology

Mechanism of Action

Tecovirimat targets and inhibits the activity of the orthopoxvirus VP37 protein (encoded by and highly conserved in all members of the orthopoxvirus genus) and blocks its interaction with cellular Rab9 GTPase and TIP47, which prevents the formation of egress competent enveloped virions necessary for cell to cell and long range dissemination of virus.

Activity in Cell Culture

In cell culture assays, the effective concentrations of tecovirimat resulting in a 50% reduction in virus-induced cytopathic effect (EC50), were 0.016-0.067 µM, 0.014-0.039 µM, 0.015 µM, and 0.009 µM, for variola, monkeypox, rabbitpox, and vaccinia viruses, respectively. Ranges given for variola and monkeypox viruses are reflective of results from multiple strains assayed.

Non-antagonistic antiviral activity of tecovirimat and brincidofovir against orthopoxviruses has been demonstrated in cell culture and animal models.

Resistance

There are no known instances of naturally occurring tecovirimat resistant orthopoxviruses, although tecovirimat resistance may develop under drug selection. Tecovirimat has a relatively low resistance barrier, and certain amino acid substitutions in the target VP37 protein can confer large reductions in tecovirimat antiviral activity. The possibility of resistance to tecovirimat should be considered in patients who either fail to respond to therapy or who develop recrudescence of disease after an initial period of responsiveness.

Cross Resistance

Cross-resistance between tecovirimat and brincidofovir is not expected based on their distinct mechanisms of action. Where tested, orthopoxvirus isolates resistant to cidofovir (the active metabolite of brincidofovir) have not been resistant to tecovirimat. Likewise, orthopoxvirus isolates resistant to tecovirimat retain their sensitivity to cidofovir.

13 NONCLINICAL TOXICOLOGY

13.1 Carcinogenesis, Mutagenesis, Impairment of Fertility

Carcinogenesis and Mutagenesis

Carcinogenicity studies have not been conducted with tecovirimat.

Tecovirimat was not genotoxic in in vitroor in vivoassays, including a bacterial reverse mutation assay, a mammalian mutagenicity assay in mouse lymphoma L5178Y/TK±cells, and in an in vivomouse micronucleus study.

Impairment of Fertility

In a fertility and early embryonic development study in mice, no effects of tecovirimat on female fertility were observed at tecovirimat exposures (AUC) approximately 24 times higher than human exposure at the RHD. In male mice, decreased male fertility associated with testicular toxicity (increased percent abnormal sperm and decreased sperm motility) was observed at 1,000 mg/kg/day (approximately 24 times the human exposure at the RHD).

13.2 Animal Toxicology and/or Pharmacology

In a repeat-dose toxicology study in dogs, convulsions (tonic and clonic) were observed in one animal within 6 hours of a single dose of 300 mg/kg (approximately 4 times higher than the highest observed human exposure at the RHD based on Cmax). Electroencephalography (EEG) findings in this animal were consistent with seizure activity during the observed convulsions. Tremors, which were considered non-adverse, were observed at 100 mg/kg/dose (similar to the highest observed human exposure at the RHD based on Cmax), although no convulsions or EEG findings were observed at this dose.

14 CLINICAL STUDIES

Overview

The effectiveness of TPOXX for treatment of smallpox disease has not been determined in humans because adequate and well-controlled field trials have not been feasible, and inducing smallpox disease in humans to study the drug’s efficacy is not ethical. Therefore, the effectiveness of TPOXX for treatment of smallpox disease was established based on results of adequate and well-controlled animal efficacy studies of non-human primates and rabbits infected with non-variola orthopoxviruses. Survival rates observed in the animal studies may not be predictive of survival rates in clinical practice.

Study Design

Efficacy studies were conducted in cynomolgus macaques infected with monkeypox virus, and New Zealand white (NZW) rabbits infected with rabbitpox virus. The primary efficacy endpoint for these studies was survival. In non-human primate studies, cynomolgus macaques were lethally challenged intravenously with 5 x 10^7plaque-forming units of monkeypox virus; tecovirimat was administered orally once daily at a dose level of 10 mg/kg for 14 days, starting at Day 4, 5 or 6 post-challenge. In rabbit studies, NZW rabbits were lethally challenged intradermally with 1,000 plaque-forming units of rabbitpox virus; tecovirimat was administered orally once daily for 14 days at a dose level of 40 mg/kg, starting at Day 4 post-challenge. The timing of tecovirimat dosing in these studies was intended to assess efficacy when treatment is initiated after animals have developed clinical signs of disease, specifically dermal pox lesions in cynomolgus macaques, and fever in rabbits. Clinical signs of disease were evident in some animals at Day 2-3 post-challenge but were evident in all animals by Day 4 post-challenge. Survival was monitored for 3-6 times the mean time to death for untreated animals in each model.

Study Results

Treatment with tecovirimat for 14 days resulted in statistically significant improvement in survival relative to placebo, except when given to cynomolgus macaques starting at Day 6 post-challenge (Table 10).

Table 10: Survival Rates in Tecovirimat Treatment Studies in Cynomolgus Macaques and NZW Rabbits Exhibiting Clinical Signs of Orthopoxvirus Disease
 | Treatment Initiationa | Survival Percentage (No. survived/n) |  | p-valueb | Survival Rate Differencec (95% CI)d
 | Treatment Initiationa | Placebo | Tecovirimat | p-valueb | Survival Rate Differencec (95% CI)d
Cynomolgus Macaques
Study 1 | Day 4 | 0% (0/7) | 80% (4/5) | 0.0038 | 80% (20.8%, 99.5%)
Study 2 | Day 4 | 0% (0/6) | 100% (6/6) | 0.0002 | 100% (47.1%, 100%)
Study 3 | Day 4 | 0% (0/3) | 83% (5/6) | 0.0151 | 83% (7.5%, 99.6%)
Study 3 | Day 5 | 0% (0/3) | 83% (5/6) | 0.0151 | 83% (7.5%, 99.6%)
Study 3 | Day 6 | 0% (0/3) | 50% (3/6) | 0.1231 | 50% (-28.3%, 90.2%)
NZW Rabbits
Study 4 | Day 4 | 0% (0/10) | 90% (9/10) | < 0.0001 | 90% (50.3%, 99.8%)
Study 5 | Day 4 | NAe | 88% (7/8) | NA | NA
aDay post-challenge tecovirimat treatment was initiated
bp-value is from 1-sided Boschloo Test (with Berger-Boos modification of gamma = 0.000001) compared to placebo
cSurvival percentage in tecovirimat treated animals minus survival percentage in placebo treated animals
dExact 95% confidence interval based on the score statistic of difference in survival rates
eA placebo control group was not included in this study.
KEY:NA = Not Applicable

16 HOW SUPPLIED/STORAGE AND HANDLING

TPOXX Capsule

How Supplied

Each TPOXX capsule contains 200 mg of tecovirimat. TPOXX capsules are hard gelatin with an opaque orange body imprinted in white ink with “SIGA” followed by the SIGA logo followed by “®”, and an opaque black cap imprinted in white ink with "ST-246®", containing white to off-white powder. Each bottle contains 42 capsules (NDC 50072-200-42) with an induction seal and child-resistant cap.

Storage and Handling

Store capsules in the original bottle at 20°C to 25°C (68°F to 77°F); excursions permitted 15°C to 30°C (59°F to 86°F) [See USP Controlled Room Temperature].

TPOXX Injection

How Supplied

TPOXX injection is supplied in a 30 mL single-dose vial as a clear, colorless to pale yellow solution for intravenous administration containing 200 mg/20 mL (10 mg/mL) of tecovirimat (NDC 50072-010-30). This solution is intended for dilution with either 0.9% (w/v) sodium chloride injection or 5% (w/v) dextrose injection solution. The vial stopper is not made with natural rubber latex. The vials are packed in cartons of seven vials. Short-term (up to 24 hours) storage and handling at an ambient temperature is acceptable.

Storage and Handling

Store TPOXX injection in a refrigerator at 2°C to 8°C (36°F to 46°F) Do not freeze.

The diluted solution(s) of TPOXX injection with either 0.9% (w/v) sodium chloride (normal saline) or 5% (w/v) dextrose solution should be used within 4 hours of preparation if stored at room temperature or within 24 hours of preparation if stored at 2°C to 8°C [see Dosage and Administration (2.5)] .

17 PATIENT COUNSELING INFORMATION

Advise the patient to read the FDA-approved patient labeling (Patient Information and Instructions for Use).

Efficacy Based on Animal Models Alone

Inform patients that the efficacy of TPOXX is based solely on efficacy studies demonstrating a survival benefit in animals and that the effectiveness of TPOXX has not been tested in humans with smallpox disease [see Clinical Studies (14)] .

Important Dosage and Administration Information

Advise patients to take TPOXX capsules as directed within 30 minutes of eating a full meal containing moderate or high fat with 6-8 oz. of water [see Clinical Pharmacology (12.3)] . Inform patients to take TPOXX for the entire duration without missing or skipping a dose [see Dosage and Administration (2)] .

Inform patients who cannot swallow capsules to refer to the Instructions for Use [see Dosage and Administration (2)] .

Drug Interactions

Inform patients that TPOXX may interact with other drugs. Advise patients to report to their healthcare provider the use of other prescription drugs [see Drug Interactions (7)] . Co-administration of TPOXX with repaglinide may cause hypoglycemia [see Warnings and Precautions (5.1) and Drug Interactions (7.1)] .

TPOXX injection: Hydroxypropyl-β-cyclodextrin, a required component of TPOXX injection, is eliminated through glomerular filtration. Therefore, in patients with severe renal impairment (defined as creatinine clearance below 30 mL/min), the use of TPOXX injection is contraindicated [see Contraindications (4)] . In patients with mild (defined as creatinine clearance 60-89 mL/min) and moderate (defined as creatinine clearance 30-59 mL/min) renal impairment, TPOXX injection should be used with caution [see Warnings and Precautions (5.2) and Use in Specific Populations (8.6)] .

Lactation

Instruct individuals with smallpox not to breastfeed their infant because of the risk of passing variola virus to the breastfed infant [see Use in Specific Populations (8.2)] .

TPOXX capsules Manufactured by:
Catalent Pharma Solutions, LLC
1100 Enterprise Drive
Winchester, KY 40391

TPOXX injection manufactured by:
Patheon Manufacturing Services LLC
5900 Martin Luther King Jr. Highway
Greenville, NC 27834

Distributed by:
SIGA Technologies, Inc.
4575 SW Research Way, Suite 110
Corvallis, OR 97333

PATIENT INFORMATION

TPOXX (Tē-Pox or Tee-pahx)
(tecovirimat)
capsules, for oral use

TPOXX (Tē-Pox or Tee-pahx)
(tecovirimat)
injection, for intravenous use

What is TPOXX?
TPOXX is a prescription medicine used to treat smallpox disease caused by a type of virus called variola virus in adults and children who weigh at least 7 pounds (3 kg).

- The effectiveness of TPOXX has been studied only in animals with orthopoxvirus diseases. There have been no human studies in people who have smallpox disease.
- The safety of TPOXX was studied in adults. There have been no studies of TPOXX in children 17 years of age and younger.
- TPOXX may not work well in people who have a weakened immune system (immunocompromised).

Who should not receive TPOXX injection?
Do not receive TPOXX injection if you or your child have severe kidney problems.TPOXX injection contains an ingredient called hydroxypropyl β-cyclodextrin which is cleared from your body through the kidneys. Tell your healthcare provider if you or your child have kidney problems because receiving TPOXX injection may not be right for you or your child.

Before taking or receiving TPOXX, tell your healthcare provider about all of your or your child’s medical conditions, including if you or your child:

- have diabetes.
- have kidney problems.
- are pregnant or plan to become pregnant. It is not known if TPOXX can harm the unborn baby. Tell your healthcare provider if you or your child become pregnant during treatment with TPOXX.
- are breastfeeding or plan to breastfeed. It is not known if TPOXX passes into your breast milk. You should not breastfeed during treatment with TPOXX.
  - You should not breastfeed if you have smallpox because of the risk of passing variola virus to the breastfed infant.
  - Talk to your healthcare provider about the best way to feed the baby during treatment with TPOXX.

Tell your healthcare provider about all of the medicines you or your child take, including prescription and over-the-counter medicines, vitamins, and herbal supplements.
Using TPOXX with certain other medicines may affect each other causing possible serious side effects. You can ask your healthcare provider or pharmacist for a list of medications that interact with TPOXX.
Especially tell your healthcare provider if you takea medicine used to treat type 2 diabetes called repaglinide.
Know the medicines you or your child take. Keep a list of your medicines to show your healthcare provider and pharmacist when you get a new medicine. Do not start taking a new medicine without telling your healthcare provider. Your healthcare provider can tell you if it is safe to take TPOXX with other medicines.

How should I take TPOXX?

- Stay under the care of your healthcare provider during treatment with TPOXX.

TPOXX capsules:

- Take TPOXX capsules exactly as your healthcare provider tells you. Do not change the dose or stop taking TPOXX without talking to your healthcare provider.
- For adults and children who weigh at least 40 kg and less than 120 kg, take 3 capsules of TPOXX 2 times a day (every 12 hours) by mouth for 14 days.
- For adults and children who weigh at least 120 kg, take 3 capsules of TPOXX 3 times a day (every 8 hours) by mouth for 14 days.
- TPOXX should be taken within 30 minutes after eating a full meal of moderate or high fat (approximately 600 calories and 25 grams of fat). Swallow capsules whole with 6 to 8 ounces of water. Talk to your healthcare provider about examples of foods that you can eat that contain about 25 grams of fat. Always take TPOXX with food.
- See the " Instructions for Use" that comes with your TPOXX capsules for instructions on how to prepare and take a dose of TPOXX if:
  - your child weighs less than 88 pounds (40 kg), or
  - you or your child have trouble swallowing TPOXX capsules.

- It is important to take TPOXX for the full 14 day course of treatment. Do not miss or skip a dose of TPOXX.
- If you miss an oral dose of TPOXX, you should take the dose as soon as possible and anytime up to 8 hours before the next scheduled dose. If less than 8 hours remain before the next scheduled dose, do not take the missed dose, and take your next dose as scheduled.
- If you take too much TPOXX, call your healthcare provider or go to the nearest hospital emergency room right away.

TPOXX Injection for Intravenous Infusion (IV)

TPOXX injection is given to you or your child by intravenous (IV) infusion into a vein slowly over 6 hours using an infusion pump by a health care provider.

What are the possible side effects of TPOXX?
TPOXX may cause serious side effects, including:

- Low blood sugar (hypoglycemia).Low blood sugar can happen when TPOXX is taken or received with repaglinide, a medicine used to treat type 2 diabetes. Tell your healthcare provider if you get any of the following symptoms of low blood sugar:

• headache
• drowsiness
• hunger
• feeling jittery or shaky

• dizziness
• confusion
• sweating

• weakness
• fast heartbeat
• irritability

The most common side effects of TPOXX capsules include:

• headache
• nausea

• stomach pain
• vomiting

The most common side effects of TPOXX injection include:

• reactions at the site of your IV infusion

These are not all the possible side effects of TPOXX.
Call your doctor for medical advice about side effects. You may report side effects to FDA at 1-800-FDA-1088.

How should I store TPOXX?

- Store TPOXX at room temperature between 68°F to 77°F (20°C to 25°C).
- Keep TPOXX in its original container.

Keep TPOXX and all other medicines out of the reach of children.

General information about the safe and effective use of TPOXX.
Medicines are sometimes prescribed for purposes other than those listed in a Patient Information leaflet. Do not use TPOXX for a condition for which it was not prescribed. Do not give TPOXX to other people, even if they have the same symptoms that you have. It may harm them. You can ask your pharmacist or healthcare provider for information about TPOXX that is written for health professionals.

What are the ingredients in TPOXX?
TPOXX capsules: 200 mg
Active ingredient:tecovirimat
Inactive ingredients:colloidal silicon dioxide, croscarmellose sodium, hydroxypropyl methyl cellulose, lactose monohydrate, magnesium stearate, microcrystalline cellulose, and sodium lauryl sulfate. The capsule shell is made of gelatin, FD&C blue No. 1, FD&C red No. 3, FD&C yellow No. 6, and titanium dioxide.
TPOXX injection: 200 mg in each 20 mL vial
Active ingredient:tecovirimat
Inactive ingredients:hydroxypropyl β-cyclodextrin and water for injection.

TPOXX capsules manufactured by:

Catalent Pharma Solutions

1100 Enterprise Drive

Winchester, KY 40391

TPOXX injection manufactured by:

Patheon Manufacturing Services LLC

5900 Martin Luther King Jr. Highway

Greenville, NC 27834

Distributed By:

SIGA Technologies, Inc.

4575 SW Research Way, Suite 110

Corvallis, OR 97333

For more information, go to www.SIGA.comor call 1-888-899-3472.

This Patient Information has been approved by the U.S. Food and Drug Administration.

Issued: 05/2022

INSTRUCTIONS FOR USE
TPOXX (Tē-Pox or Tee-pahx)
(tecovirimat)
capsules, for oral use

This Instructions for Use contains information on how to prepare and give a dose of TPOXX capsules to children who weigh 28 pounds (13 kg) to less than 88 pounds (40 kg) or adults or children who have trouble swallowing TPOXX capsules whole.

Read this Instructions for Use before taking TPOXX capsules. There may be new information. This Instructions for Use does not take the place of talking to your healthcare provider about your medicinal condition or treatment.

Step 1:Gather the supplies you need to prepare a dose of TPOXX:

- 1 bottle of TPOXX (1 capsule = 200 mg of medicine)
- 1 tablespoon
- 1 small bowl or cup
- Your choice of liquid or soft food:
  - Liquid such as milk, chocolate milk or infant formula
  - Soft food such as applesauce or yogurt

Step 2:Find the weight of the person taking the medicine on the TPOXX Dosing Table (see Figure A).

Step 3:Find the prescribed dose in the same row as the weight of the person taking the medicine on the TPOXX Dosing Table (see Figure A).

Step 4:

- Get a small bowl or cup and place it on a flat surface.
- Add 2 tablespoons (30 mL) of liquid or soft food to the bowl or cup.

Step 5:Find the number of TPOXX capsules needed in the same row as the weight of the person taking the medicine on the TPOXX Dosing Table (see Figure A).

- Take out the correct number of TPOXX capsules from the bottle.

Step 6:Hold the TPOXX capsule in a sideways (horizontal) position directly over the bowl or cup to make sure none of the medicine is lost.

- Hold the ends of the TPOXX capsule between the thumb and index (pointer) finger of both hands.
- Gently and slowly twist the ends of the capsule and pull it apart. Empty the contents of the capsule into the bowl or cup. Repeat this for each capsule that is needed for the total prescribed dose.
- Throw away the empty capsule shells.

Step 7:Use the tablespoon to mix together the capsule contents and the liquid or soft food.

- The powder may not completely dissolve.
- The TPOXX medicine mixture is now ready to take.

Step 8:Swallow the TPOXX medicine mixture. All the TPOXX medicine mixtureshould be swallowed to make sure the entire dose it taken.

- The TPOXX mixture must be taken within 30 minutes after a meal containing approximately 25 grams of fat andwithin 30 minutes after mixing it.
- For people weighing 28 pounds (13 kg) to less than 264 pounds (120 kg), TPOXX medicine mixture should be given 2 times a day (every 12 hours), by mouth, for 14 days.
- For people weighing 264 pounds (120 kg) and above, TPOXX medicine mixture should be given 3 times a day (every 8 hours), by mouth, for 14 days.

TPOXX Dosing Table (Figure A)
Body Weight | Prescribed Dose | Amount of Liquid or Soft Food | Number of Capsules | Food and Medicine Mixture Instructions
28 pounds (13 kg) to less than 55 pounds (25 kg)a | 200 mg (1 capsule) Every 12 hours | 2 tablespoons | 1 TPOXX capsule | Mix entire contents of 1 TPOXX capsule with 2 tablespoons of liquid or soft food.
55 pounds (25 kg) to less than 88 pounds (40 kg)a | 400 mg (2 capsules) Every 12 hours | 2 tablespoons | 2 TPOXX capsules | Mix entire contents of 2 TPOXX capsules with 2 tablespoons of liquid or soft food.
88 pounds (40 kg) to less than 265 pounds (120 kg)a | 600 mg (3 capsules) Every 12 hours | 2 tablespoons | 3 TPOXX capsules | Mix entire contents of 3 TPOXX capsules with 2 tablespoons of liquid or soft food.
265 pounds (120 kg) and aboveb | 600 mg (3 capsules) Every 8 hours | 2 tablespoons | 3 TPOXX capsules | Mix entire contents of 3 TPOXX capsules with 2 tablespoons of liquid or soft food.
aGiven twice daily every 12 hours, by mouth, for 14 days.
bGiven three times a day every 8 hours, by mouth, for 14 days.

How should I store TPOXX Capsules?

- Store TPOXX at room temperature between 68°F to 77°F (20°C to 25°C).
- Keep TPOXX in its original container.

Keep TPOXX and all medicines out of the reach of children.

TPOXX capsules Manufactured by:
Catalent Pharma Solutions
1100 Enterprise Drive
Winchester, KY 40391

TPOXX injection manufactured by:
Patheon Manufacturing Services LLC
5900 Martin Luther King Jr. Highway
Greenville, NC 27834

Distributed by:
SIGA Technologies, Inc.
4575 SW Research Way, Suite 110
Corvallis, OR 97333

This Instructions for Use has been approved by the U.S. Food and Drug Administration.

Revised: 05/2022